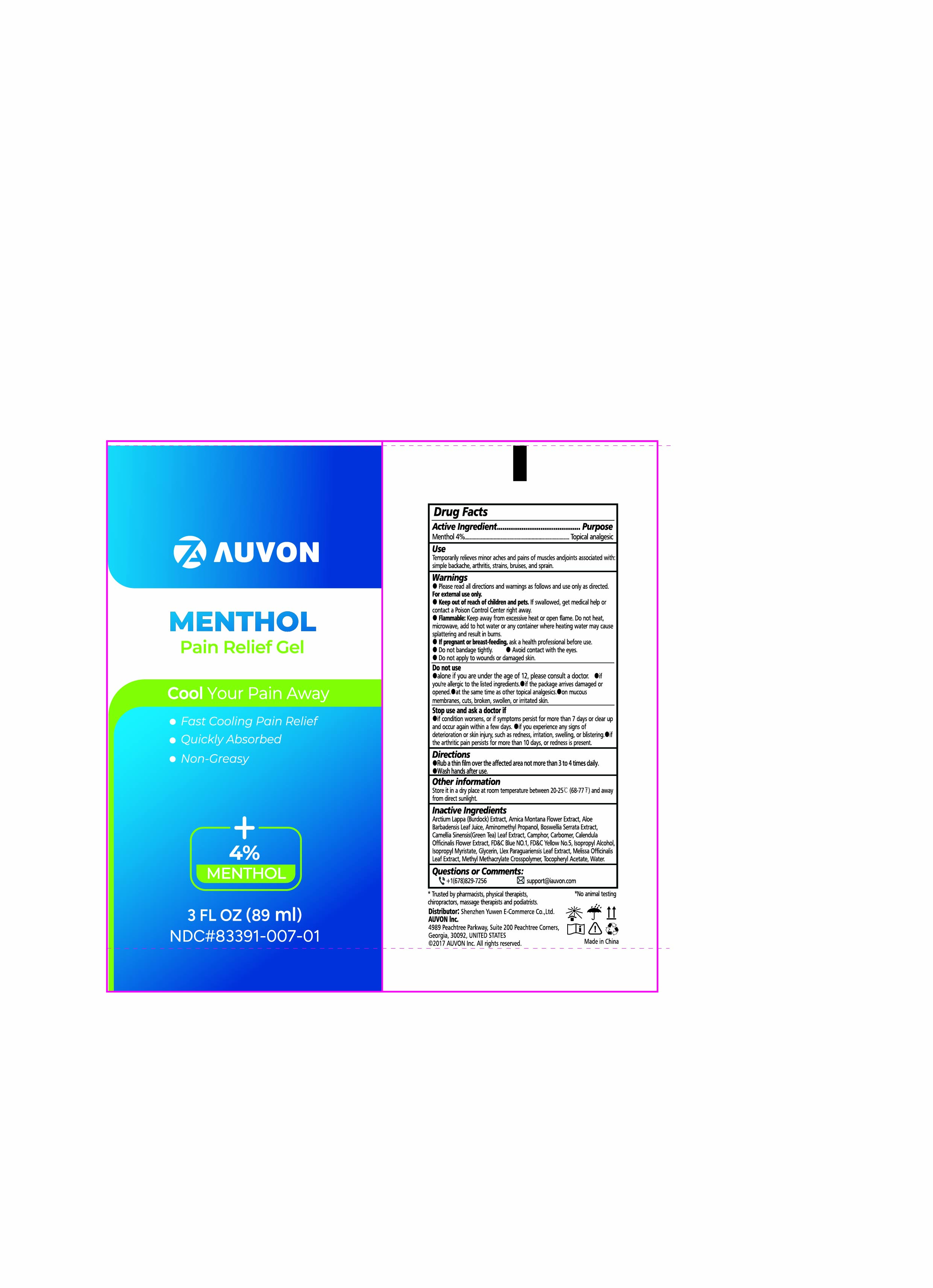 DRUG LABEL: Auvon 4% Menthol Pain Relief Gel
NDC: 83391-007 | Form: GEL
Manufacturer: SHENZHEN YUWEN E-COMMERCE CO., LTD.
Category: otc | Type: HUMAN OTC DRUG LABEL
Date: 20250314

ACTIVE INGREDIENTS: LEVOMENTHOL 0.04 mg/1 mL
INACTIVE INGREDIENTS: ARNICA MONTANA FLOWER WATER; ALOE BARBADENSIS LEAF; CARBOMER; ILEX PARAGUARIENSIS LEAF; AMINOMETHYL PROPANOL; .ALPHA.-TOCOPHEROL ACETATE; ISOPROPYL ALCOHOL; WATER; FD&C BLUE NO. 1; FD&C YELLOW NO. 5; BOSWELLIA SERRATA OIL; CALENDULA OFFICINALIS FLOWER; ARCTIUM LAPPA WHOLE; ISOPROPYL MYRISTATE; CAMELLIA SINENSIS LEAF OIL; METHYL METHACRYLATE/GLYCOL DIMETHACRYLATE CROSSPOLYMER; GLYCERIN; MELISSA OFFICINALIS LEAF OIL; CAMPHOR (NATURAL)

83391-007

Auvon 4% Menthol Pain Relief Gel

ACTIVE INGREDIENT

Menthol 4%

PURPOSE

Topical Analgestic

INDICATIONS AND USAGE

Temporary relief from minor aches and paons of sore muscles and joints

WARNINGS

For external use only

DO NOT USE

If you are under 12 years of age

If you are allergic to the listed ingredients

If you are pregnent or breast feeding

On wounds, cuts, damaged/broken/irritated skin

WHEN USING

■ Use only as directed

■ Read and follow all directions and warnings on this label

STOP USE

You are experiencing pain, swelling or blistering

Redness is persent or irritation develops

Symptoms persist for more than 7 days or clear up and occur again within a few days

KEEP OUT OF REACH OF CHILDREN

If swallowed, get medical help or contact a Poison Control Center right away.

DOSAGE AND ADMINISTRATION

Clean and dry the patch application area (no wound or hair), pull to separate the film, peel off one side of the film, apply the exposed patch to the skin, peel off the other side of the film, and press the patch firmly ■ Do not repeatedly use or repeatedly reapply the patch as far as possible

Use in te affected area no more than 4 times daily

Wash hands with cool water after use

STORAGE AND HANDLING

Store it in a dray place at a room temperature between 20-25°c and away from direct sunlight

INACTIVE INGREDIENT

Arctium Lappa (Burdock) Extract

Arnica Montana Flower Extract

Aloe Barbadensis Leaf Juice

Aminomethyl Propanol

Boswellia Serrata Extract

Camellia Sinensis(Green Tea) Leaf Extract

Camphor

Carbomer

Calendula Officinalis Flower Extract

FD&C Blue NO.1

FD&C Yellow No.5

Isopropyl Alcohol

Isopropyl Myristate,

Glycerin

Llex Paraguariensis Leaf Extract

Melissa Officinalis Leaf Extract

Methyl Methacrylate Crosspolymer

Tocopheryl Acetate

Water